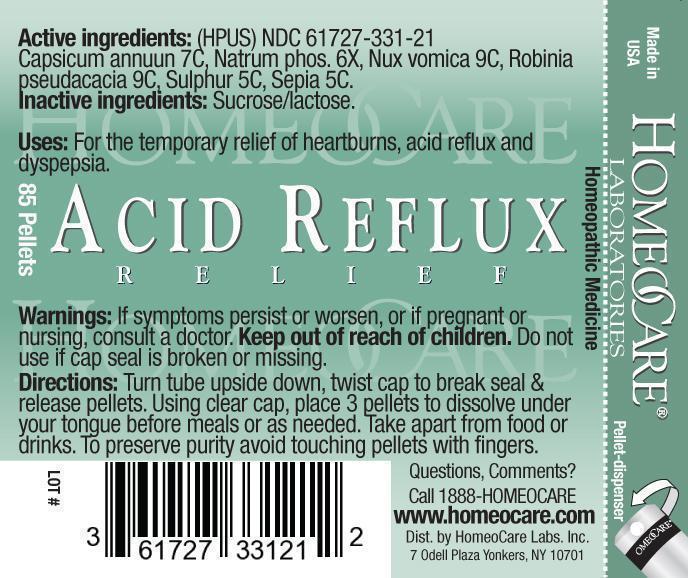 DRUG LABEL: Acid Reflux Relief
NDC: 61727-331 | Form: PELLET
Manufacturer: Homeocare Laboratories
Category: homeopathic | Type: HUMAN OTC DRUG LABEL
Date: 20190320

ACTIVE INGREDIENTS: CAPSICUM 7 [hp_C]/4 g; SODIUM PHOSPHATE, DIBASIC, HEPTAHYDRATE 6 [hp_X]/4 g; STRYCHNOS NUX-VOMICA SEED 9 [hp_C]/4 g; ROBINIA PSEUDOACACIA BARK 9 [hp_C]/4 g; SULFUR 5 [hp_C]/4 g; SEPIA OFFICINALIS JUICE 5 [hp_C]/4 g
INACTIVE INGREDIENTS: SUCROSE; LACTOSE

Acid Reflux Relief

Active Ingredients:

Capiscuum Annuun 7C, Natrum Phos 6X, Nux Vomica 9C, Robinia Pseudaccia 9C, Sulphur 5C, Sepia 5C.

Purpose:

For the temporary relief of heartburns, acid reflux and dyspepsia.

Keep out of reach of children.

Indications & Usage:

Turn tube upside down, twist cap to break seal & release pellets. Using clear cap, place 3 pellets to dissolve under your tongue before meals or as needed. Take apart from food or drinks. To preserve purity avoid touching pellets with fingers.

Warnings:

If symptoms persist or worsen, or if pregnant or nursing, consult a doctor. Keep out of reach of children. Do not use if cap seal is broken or missing.

Dosage & Administration:

Turn tube upside down, twist cap to break seal & release pellets. Using clear cap, place 3 pellets to dissolve under your tongue before meals or as needed. Take apart from food or drinks. To preserve purity avoid touching pellets with fingers.

Inactive Ingredients:

Sucrose/lactose.